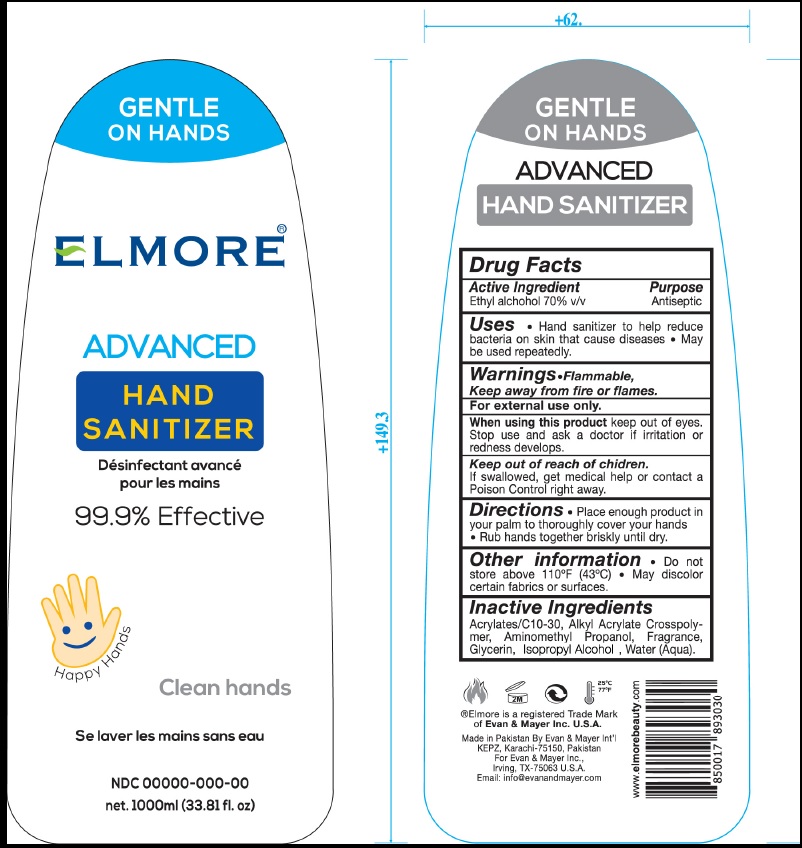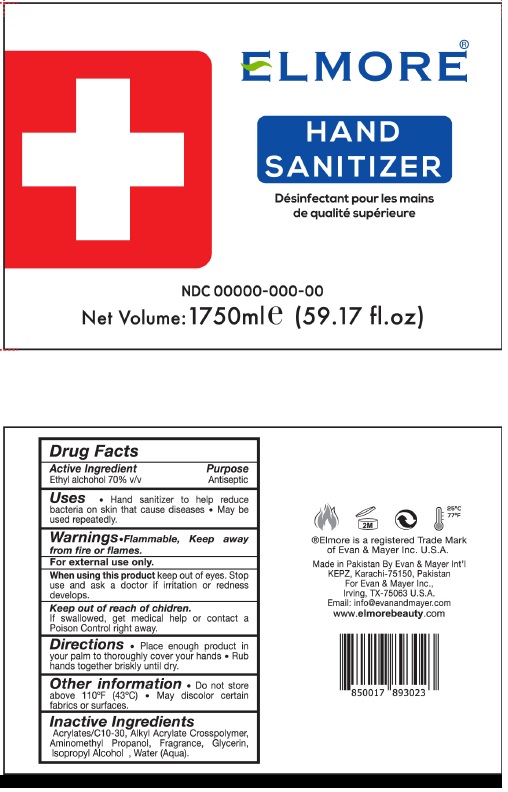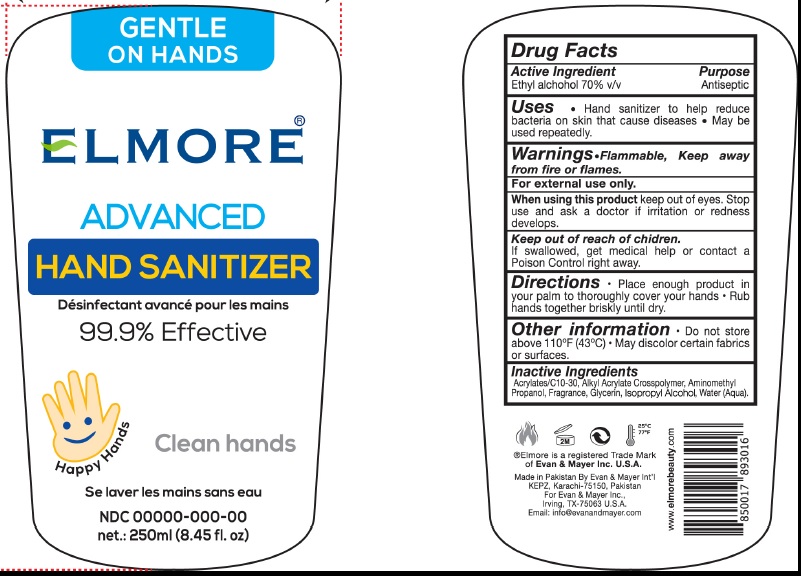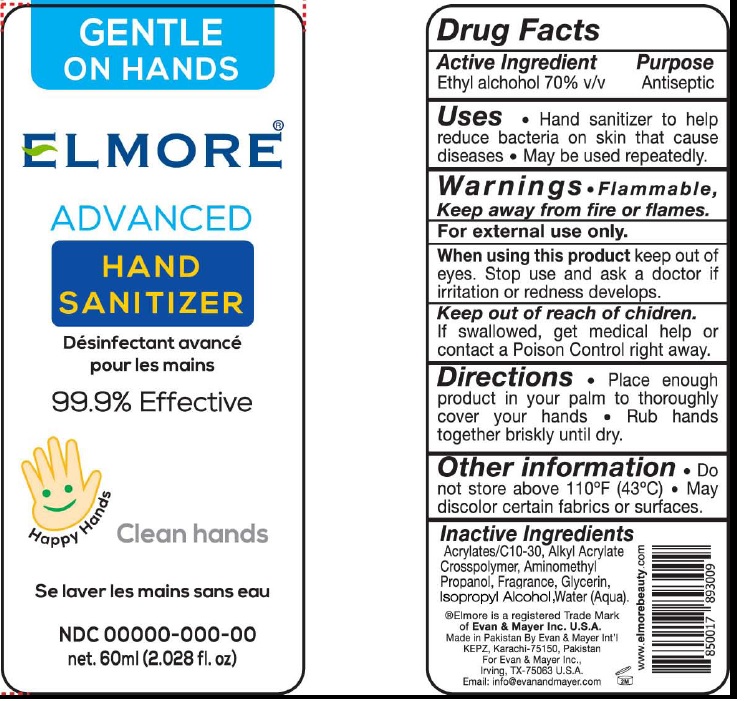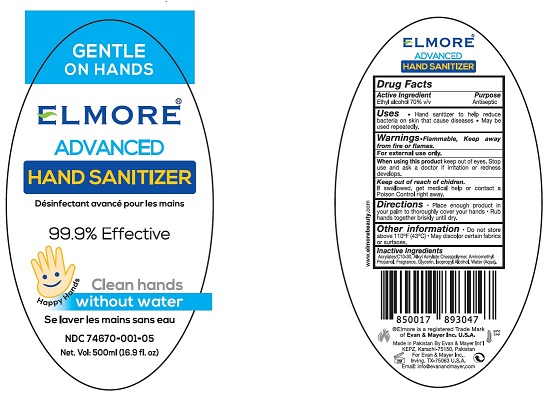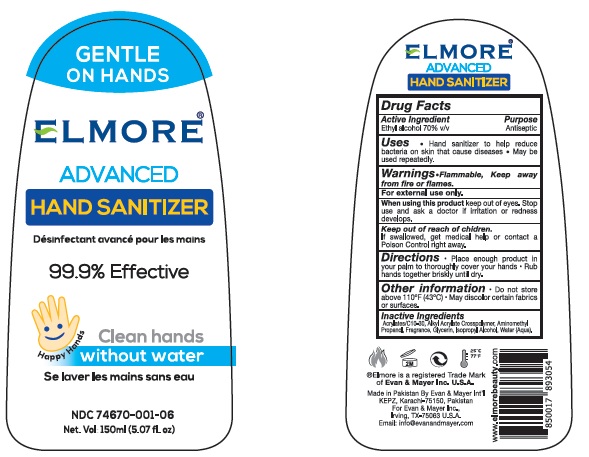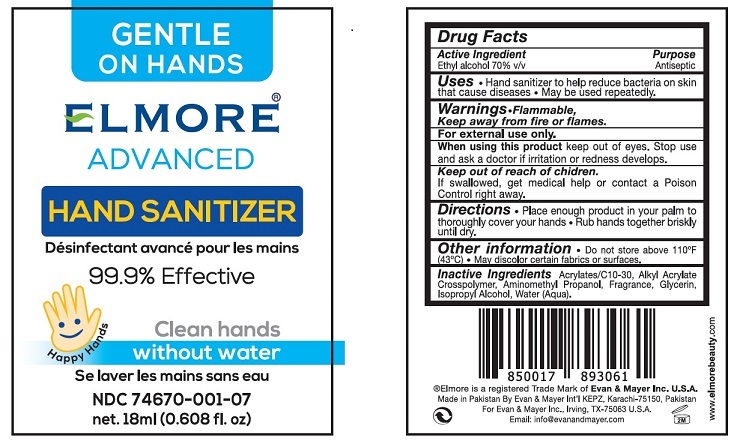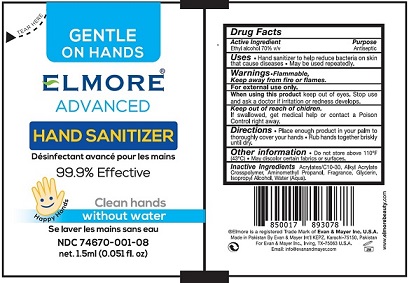 DRUG LABEL: Elmore Hand Sanitizer
NDC: 74670-001 | Form: GEL
Manufacturer: Evan and Mayer International
Category: otc | Type: HUMAN OTC DRUG LABEL
Date: 20200427

ACTIVE INGREDIENTS: ALCOHOL 70 mL/100 mL
INACTIVE INGREDIENTS: CARBOMER INTERPOLYMER TYPE A (ALLYL SUCROSE CROSSLINKED); AMINOMETHYLPROPANOL; GLYCERIN; ISOPROPYL ALCOHOL; WATER

Elmore Hand Sanitizer

Drug Facts

Active Ingredient
Ethyl alchohol 70%

Purpose
Antiseptic

INDICATIONS AND USAGE

Uses • Hand sanitizer to help
reduce bacteria on skin that cause
diseases. • May be used repeatedly.

Warnings •Flammable,
Keep away from fire or flames.

For external use only.

When using this product keep out of
eyes. Stop use and ask a doctor if
irritation or redness develops.

Keep out of reach of chidren.
If swallowed, get medical help or
contact a Poison Control right away.

DOSAGE AND ADMINISTRATION

Directions • Place enough
product in your palm to thoroughly
cover your hands • Rub hands
together briskly until dry.

Other information • Do
not store above 110°F (43°C) • May
discolor certain fabrics or surfaces.

Inactive Ingredients
Acrylates/C10-30, Alkyl Acrylate
Crosspolymer, Aminomethyl
Propanol, Fragrance, Glycerin,
Isopropyl Alcohol, Water (Aqua).

Principal Display Label

GENTLE
ON HANDS

ELMORE®

ADVANCED
HAND SANITIZER

Desinfectant avance
pour les mains

99.9% Effective

Clean hands

Se laver les mains sans eau

NDC 00000-000-00
net. 60ml (2.028 fl.oz)

®Elmore is a registered Trade Mark
of Evan & Mayer Inc. U.S.A.
Made in Pakistan By Evan & Mayer Int'I
KEPZ, Karachi-75150, Pakistan
For Evan & Mayer Inc.,
Irving, TX-75063 U.S.A.
Email: info@evanandmayer.com

www.elmorebeauty.com

60 mL Bottle

250 mL Bottle

1000 mL Bottle

1750 mL Bottle

500 mL Bottle

150 mL Bottle

18 mL Bottle

1.5 mL Bottle

res